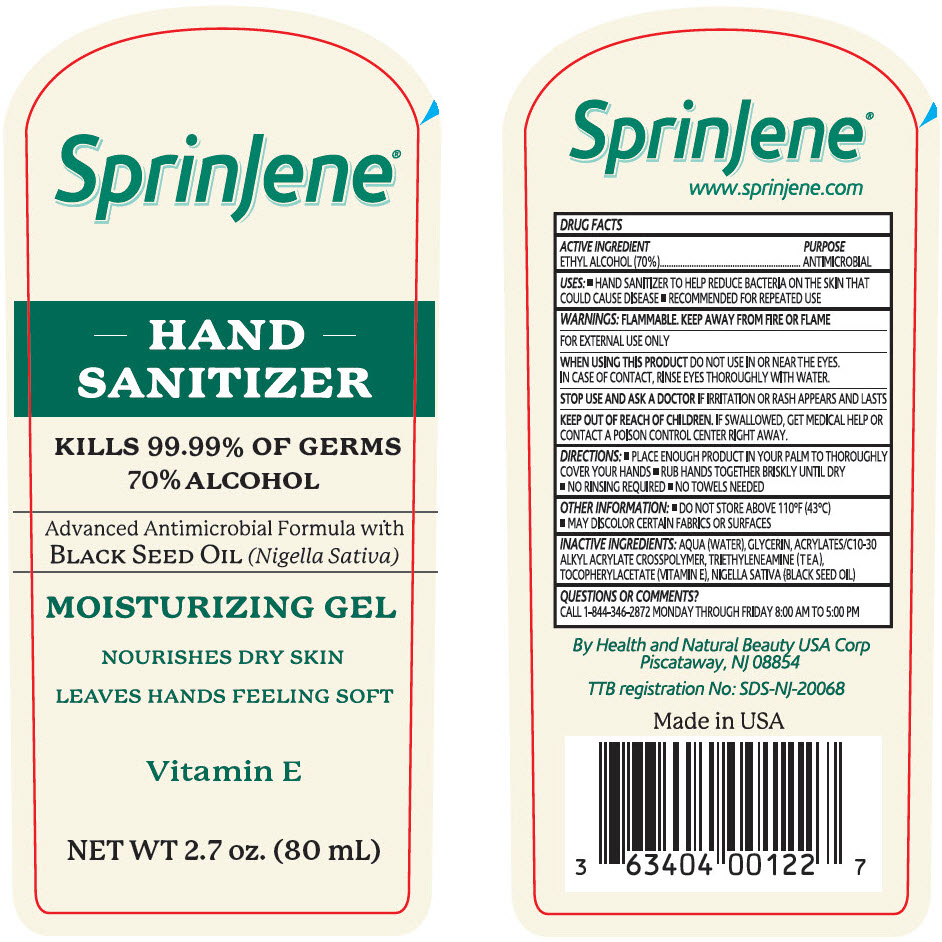 DRUG LABEL: SprinJene
NDC: 63404-0720 | Form: GEL
Manufacturer: Health and Natural Beauty USA Corp
Category: otc | Type: HUMAN OTC DRUG LABEL
Date: 20200722

ACTIVE INGREDIENTS: ALCOHOL 70 mL/100 mL
INACTIVE INGREDIENTS: WATER; Glycerin; Carbomer Interpolymer Type A (Allyl Sucrose Crosslinked); TRIETHYLENE AMINE; .ALPHA.-TOCOPHEROL ACETATE

SprinJene®

DRUG FACTS

ACTIVE INGREDIENT

ETHYL ALCOHOL (70%)

PURPOSE

ANTIMICROBIAL

USES

- HAND SANITIZER TO HELP REDUCE BACTERIA ON THE SKIN THAT COULD CAUSE DISEASE
- RECOMMENDED FOR REPEATED USE

WARNINGS

FLAMMABLE. KEEP AWAY FROM FIRE OR FLAME

FOR EXTERNAL USE ONLY

WHEN USING THIS PRODUCT DO NOT USE IN OR NEAR THE EYES. IN CASE OF CONTACT, RINSE EYES THOROUGHLY WITH WATER.

STOP USE AND ASK A DOCTOR IF IRRITATION OR RASH APPEARS AND LASTS

KEEP OUT OF REACH OF CHILDREN. IF SWALLOWED, GET MEDICAL HELP OR CONTACT A POISON CONTROL CENTER RIGHT AWAY.

DIRECTIONS

- PLACE ENOUGH PRODUCT IN YOUR PALM TO THOROUGHLY COVER YOUR HANDS
- RUB HANDS TOGETHER BRISKLY UNTIL DRY
- NO RINSING REQUIRED
- NO TOWELS NEEDED

OTHER INFORMATION

- DO NOT STORE ABOVE 110°F (43°C)
- MAY DISCOLOR CERTAIN FABRICS OR SURFACES

INACTIVE INGREDIENTS

AQUA (WATER), GLYCERIN, ACRYLATES/C10-30 ALKYL ACRYLATE CROSSPOLYMER, TRIETHYLENEAMINE (TEA), TOCOPHERYLACETATE (VITAMIN E), NIGELLA SATIVA (BLACK SEED OIL)

QUESTIONS OR COMMENTS?

CALL 1-844-346-2872 MONDAY THROUGH FRIDAY 8:00 AM TO 5:00 PM

PRINCIPAL DISPLAY PANEL - 80 mL Bottle Label

SprinJene®

HAND
SANITIZER

KILLS 99.99% OF GERMS
70% ALCOHOL

Advanced Antimicrobial Formula with
BLACK SEED OIL (Nigella Sativa)

MOISTURIZING GEL

NOURISHES DRY SKIN

LEAVES HANDS FEELING SOFT

Vitamin E

NET WT 2.7 oz. (80 mL)